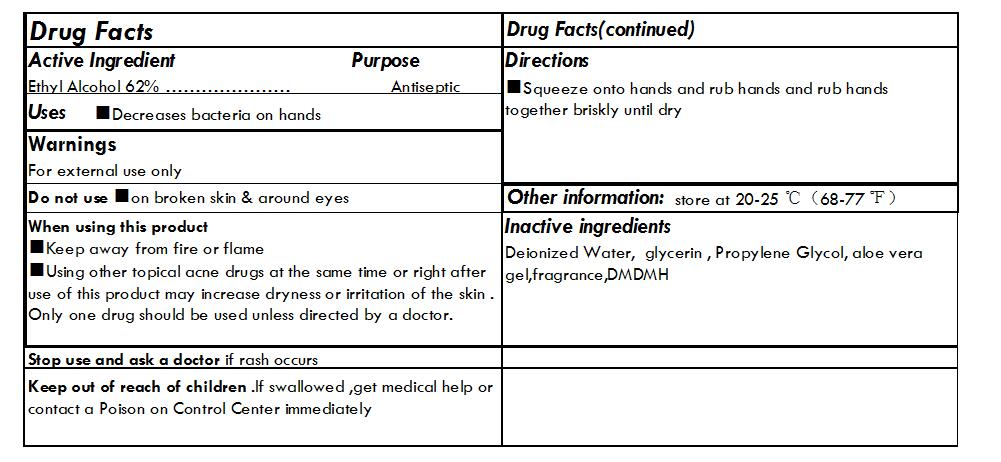 DRUG LABEL: HAND SANITIZER
NDC: 71011-003 | Form: GEL
Manufacturer: NingBo Huize Commodity Co.,Ltd.
Category: otc | Type: HUMAN OTC DRUG LABEL
Date: 20180106

ACTIVE INGREDIENTS: ALCOHOL 62 mL/100 mL
INACTIVE INGREDIENTS: WATER; GLYCERIN; DMDM HYDANTOIN; ALOE VERA LEAF; PROPYLENE GLYCOL DIACETATE

HAND SANITIZER

Active Ingredient

Ethyl Alcohol 62%

Purpose

Antiseptic

Use

Decreases bacteria on hands

Warning

for external use only

Do not use on broken skin & around eyes

When using this product
■Keep away from fire or flame
■Using other topical acne drugs at the same time or right after use of this product may increase dryness or irritation of the skin . Only one drug should be used unless directed by a doctor.

Keep out of reach of children .If swallowed ,get medical help or contact a Poison on Control Center immediately

Directions

Squeeze onto hands and rub hands and rub hands together briskly until dry

INACTIVE INGREDIENT

Deionized Water, glycerin , Propylene Glycol, aloe vera gel,fragrance,DMDMH